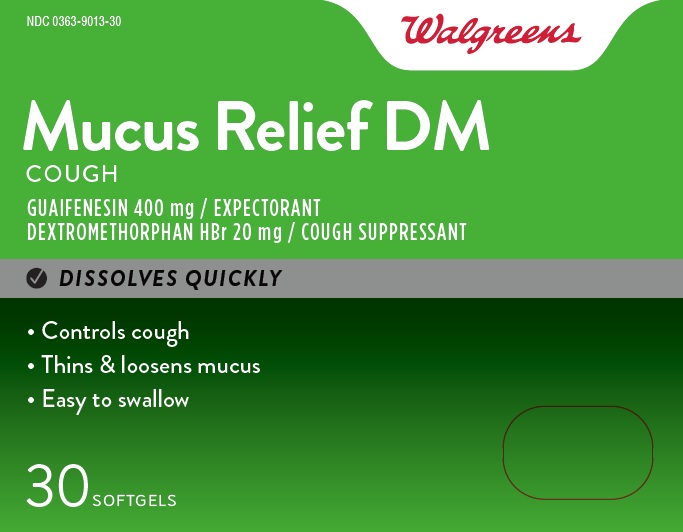 DRUG LABEL: MUCUS RELIEF DM
NDC: 0363-9013 | Form: CAPSULE, LIQUID FILLED
Manufacturer: Walgreens
Category: otc | Type: HUMAN OTC DRUG LABEL
Date: 20260116

ACTIVE INGREDIENTS: GUAIFENESIN 400 mg/1 1; DEXTROMETHORPHAN HYDROBROMIDE 20 mg/1 1
INACTIVE INGREDIENTS: GLYCERIN; GELATIN; POLYETHYLENE GLYCOL 400; POVIDONE K30; PROPYLENE GLYCOL; WATER; SODIUM HYDROXIDE; SORBITOL; SORBITAN; TITANIUM DIOXIDE

MUCUS RELIEF DM

Drug Facts

ACTIVE INGREDIENT

Active ingredient (in each softgel) | Purposes
Guaifenesin 400mg | Expectorant
Dextromethorphan HBr 20mg | Cough Suppressant

Uses

- helps loosen phlegm (mucus)
- helps thin bronchial secretions to make coughs more productive

Warnings

Do not use

- If you are now taking a prescription monoamine oxidase inhibitor (MAOI) (certain drugs for depression, psychiatric, or emotional conditions, or Parkinson's disease), or for 2 weeks after stopping the MAOI drug. If you do not know if your prescription drug contains an MAOI, ask a doctor or pharmacist before taking this product.

Ask Doctor before use if you have

- cough accompanied by excessive phlegm (mucus)
- persistent or chronic cough such as occurs with smoking, asthma, chronic bronchitis or emphysema

When using this product

- do not exceed recommended dosage
- do not use for more than 7 days

Stop use and ask a doctor if

- cough lasts for more than 7 days, recurs, or is accompanied by fever, rash, or persistent headache. These could be signs of a serious condition.

PREGNANCY OR BREAST FEEDING

If pregnant or breast-feeding ask a health professional before use

Keep Out of Reach of Children In case of accidental overdose, get medical help or contact a Poison Control Center right away.

Directions

Adults and children 12 years of age and older:

- Take with a full glass of water.
- Take 1 softgel every 4 hours with a full glass of water while symptoms persist. Do not exceed 6 doses in 24 hours.
- Children under 12 years of age: do not use

Other information

- store at 25°C (77°F) excursions between 15° - 30°C (59° - 86°F)
- keep in a dry place and do not expose to heat
- you may report side effects to 1-888-333-9792

Inactive Ingredients

gelatin, glycerin, polyethylene glycol, povidone, propylene glycol, purified water, sodium hydroxide*, sorbitol sorbitan
solution, titanium dioxide
*may contain this ingredient

Questions or comments?

1-888-333-9792

PRINCIPAL DISPLAY PANEL

Walgreens

Mucus Relief DM

COUGH

GUAIFENESIN 400 mg/EXPECTORANT
DEXTROMETHORPHAN HBr 20 mg/COUGH SUPPRESSANT

DISSOLVES QUICKLY

Controls cough
Thins & loosens mucus
30 SOFTGELS